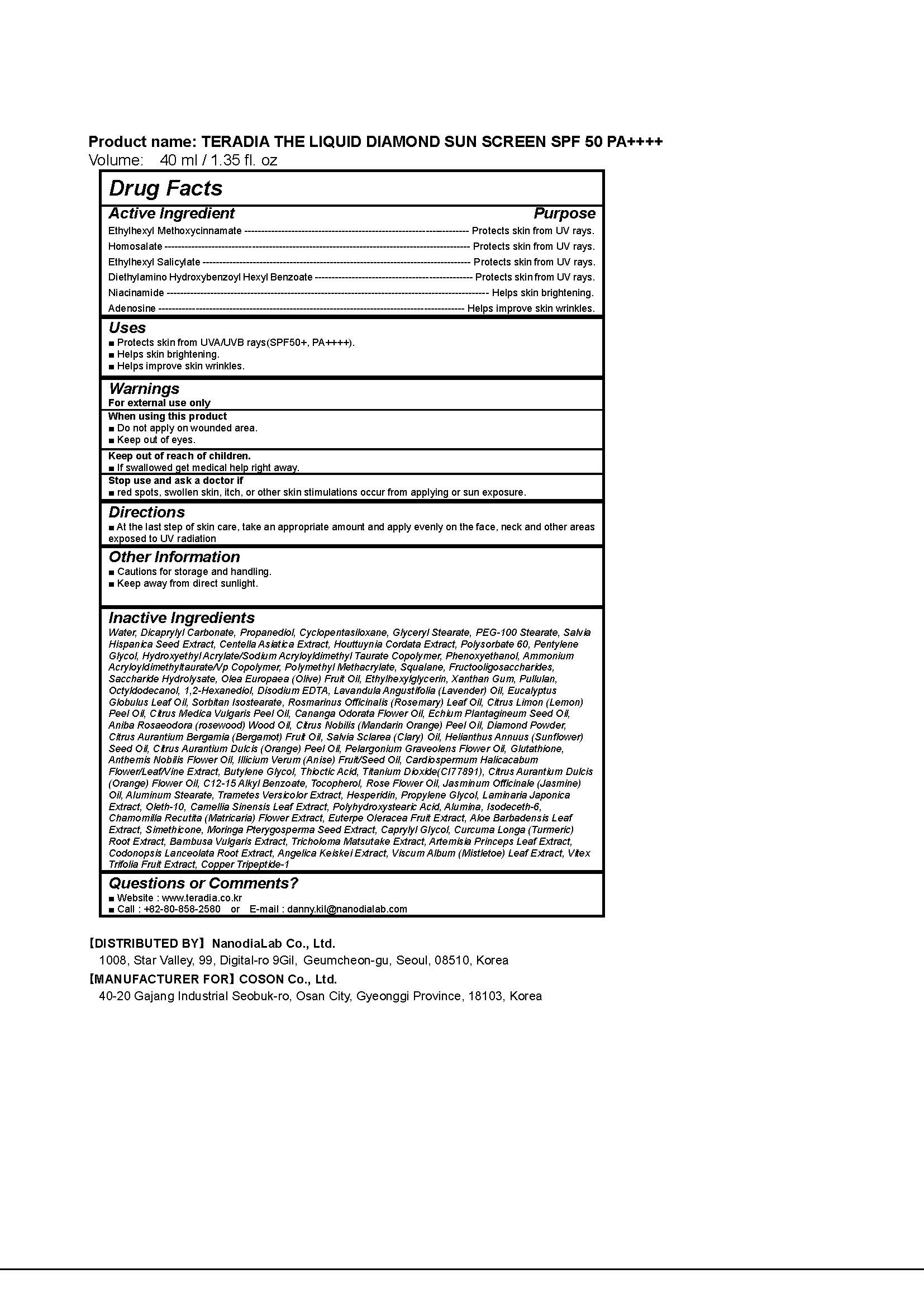 DRUG LABEL: TERADIA THE LIQUIDDIAMOND SUNSCREEN SPF50
NDC: 71483-0001 | Form: CREAM
Manufacturer: NanoDia Lab Co Ltd
Category: otc | Type: HUMAN OTC DRUG LABEL
Date: 20181218

ACTIVE INGREDIENTS: OCTINOXATE 7 g/100 mL; HOMOSALATE 6 g/100 mL; OCTISALATE 4.5 g/100 mL
INACTIVE INGREDIENTS: ADENOSINE; NIACINAMIDE

Drug Facts

ACTIVE INGREDIENT

Octinoxate, Homosalate, Octisalate

INACTIVE INGREDIENT

Niacinamide, Adenosine

PURPOSE

Sunscreen, Anti-Wrinkle, Whitening

keep out of reach of the children

INDICATIONS AND USAGE

At the last step of skin care, take an appropriate amount and apply evenly on the face, neck and other areas exposed to UV radiation

WARNINGS

1. Do not use in the following cases(Eczema and scalp wounds)
2.Side Effects
1)Due to the use of this druf if rash, irritation, itching and symptopms of hypersnesitivity occur dicontinue use and consult your phamacisr or doctor
3.General Precautions
1)If in contact with the eyes, wash out thoroughty with water If the symptoms are servere, seek medical advice immediately
2)This product is for exeternal use only. Do not use for internal use
4.Storage and handling precautions
1)If possible, avoid direct sunlight and store in cool and area of low humidity
2)In order to maintain the quality of the product and avoid misuse
3)Avoid placing the product near fire and store out in reach of children

DOSAGE AND ADMINISTRATION

for external use only